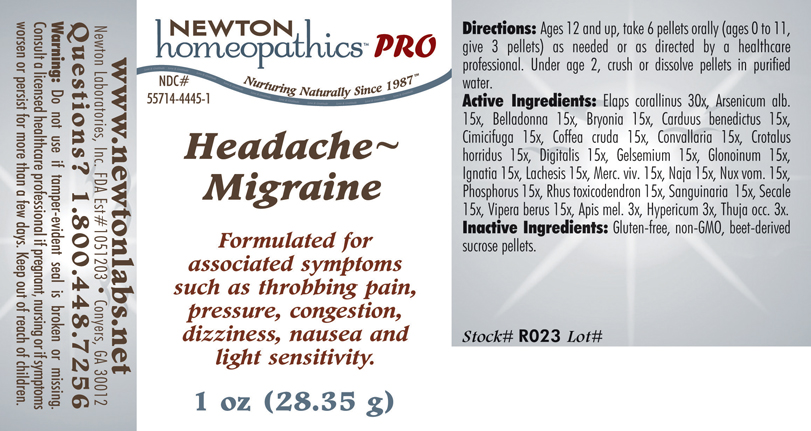 DRUG LABEL: Headache - Migraine 
NDC: 55714-4445 | Form: PELLET
Manufacturer: Newton Laboratories, Inc.
Category: homeopathic | Type: HUMAN PRESCRIPTION DRUG LABEL
Date: 20110601

ACTIVE INGREDIENTS: Micrurus Corallinus Venom 30 [hp_X]/1 g; Arsenic Trioxide 15 [hp_X]/1 g; Atropa Belladonna 15 [hp_X]/1 g; Bryonia Alba Root 15 [hp_X]/1 g; Centaurea Benedicta 15 [hp_X]/1 g; Black Cohosh 15 [hp_X]/1 g; Arabica Coffee Bean 15 [hp_X]/1 g; Convallaria Majalis 15 [hp_X]/1 g; Crotalus Horridus Horridus Venom 15 [hp_X]/1 g; Digitalis 15 [hp_X]/1 g; Gelsemium Sempervirens Root 15 [hp_X]/1 g; Nitroglycerin 15 [hp_X]/1 g; Strychnos Ignatii Seed 15 [hp_X]/1 g; Lachesis Muta Venom 15 [hp_X]/1 g; Mercury 15 [hp_X]/1 g; Naja Naja Venom 15 [hp_X]/1 g; Strychnos Nux-vomica Seed 15 [hp_X]/1 g; Phosphorus 15 [hp_X]/1 g; Toxicodendron Pubescens Leaf 15 [hp_X]/1 g; Sanguinaria Canadensis Root 15 [hp_X]/1 g; Claviceps Purpurea Sclerotium 15 [hp_X]/1 g; Vipera Berus Venom 15 [hp_X]/1 g; Apis Mellifera 3 [hp_X]/1 g; Hypericum Perforatum 3 [hp_X]/1 g; Thuja Occidentalis Leafy Twig 3 [hp_X]/1 g
INACTIVE INGREDIENTS: Sucrose

Headache - Migraine

INDICATIONS & USAGE SECTION

HEADACHE - MIGRAINE Formulated for associated symptoms such as throbbing pain, pressure, congestion, dizziness, nausea and light sensitivity.

DOSAGE & ADMINISTRATION SECTION

Directions: Ages 12 and up, take 6 pellets orally (ages 0 to 11, give 3 pellets) as needed or as directed by a healthcare professional. Under age 2, crush or dissolve pellets in purified water.

ACTIVE INGREDIENT SECTION

Elaps corallinus 30x, Arsenicum alb. 15x, Belladonna 15x, Bryonia 15x, Carduus benedictus 15x, Cimicifuga 15x, Coffea cruda 15x, Convallaria 15x, Crotalus horridus 15x, Digitalis 15x, Gelsemium 15x, Glonoinum 15x, Ignatia 15x, Lachesis 15x, Merc. viv. 15x, Naja 15x, Nux vom. 15x, Phosphorus 15x, Rhus toxicodendron 15x, Sanguinaria 15x, Secale 15x, Vipera berus 15x, Apis mel. 3x, Hypericum 3x, Thuja occ. 3x.

PURPOSE SECTION

Formulated for associated symptoms such as throbbing pain, pressure, congestion, dizziness, nausea and light sensitivity.

INACTIVE INGREDIENT SECTION

Inactive Ingredients: Gluten-free, non-GMO, beet-derived sucrose pellets.

QUESTIONS? SECTION

www.newtonlabs.net Newton Laboratories, Inc. FDA Est # 1051203 - Conyers, GA 30012
Questions? 1.800.448.7256

WARNINGS SECTION

Warning: Do not use if tamper - evident seal is broken or missing. Consult a licensed healthcare professional if pregnant, nursing or if symptoms worsen or persist for more than a few days. Keep out of reach of children.

PREGNANCY OR BREAST FEEDING SECTION

Consult a licensed healthcare professional if pregnant or nursing or if symptoms worsen or persist for more than a few days.

KEEP OUT OF REACH OF CHILDREN SECTION

Keep out of reach of children.